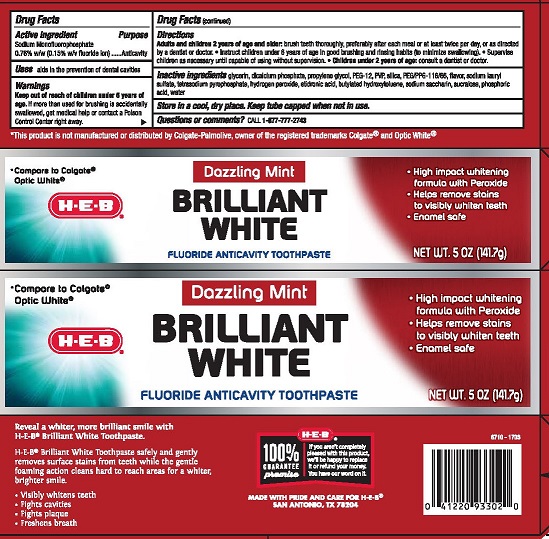 DRUG LABEL: HEB

NDC: 37808-896 | Form: PASTE, DENTIFRICE
Manufacturer: HEB
Category: otc | Type: HUMAN OTC DRUG LABEL
Date: 20230111

ACTIVE INGREDIENTS: SODIUM MONOFLUOROPHOSPHATE 0.76 g/100 g
INACTIVE INGREDIENTS: GLYCERIN; SODIUM PYROPHOSPHATE; POLYETHYLENE GLYCOL, UNSPECIFIED; PROPYLENE GLYCOL; SACCHARIN SODIUM; SUCRALOSE; BUTYLATED HYDROXYTOLUENE; PEG/PPG-116/66 COPOLYMER; PHOSPHORIC ACID; CALCIUM PHOSPHATE, DIBASIC, ANHYDROUS; HYDRATED SILICA; SODIUM LAURYL SULFATE; ETIDRONIC ACID; WATER; HYDROGEN PEROXIDE; CROSPOVIDONE, UNSPECIFIED

HEB Brilliant White Dazzling Mint

Drug Facts

Active ingredient

Sodium Monofluorophosphate 0.76% w/w (0.15% w/v fluoride ion)

Purpose

Anticavity

INDICATIONS AND USAGE

Uses aids in the prevention of dental caviites

Warnings

Keep out of reach of children under 6 years of age. If more than used for brushing is accidentally swallowed, get medical help or contact a Poison Control Center right away.

Directions

Adults and children 2 years of age and older: brush teeth thorughly preferably after each meal or at least twice per day, or as directed by a dentist or doctor.

- Instruct children under 6 years of age in good brushing and rinsing habits (to avoid swallowing).
- Supervise children as necessary until capable of using without supervision.
- Children under 2 years of age: consult a dentist or doctor.

INACTIVE INGREDIENT

Inactive ingredients glycerin, dicalcium phosphate, propylene glycol, PEG-12, PVP, silica, PEG/PPG 116/66 copolymer, flavor, sodium lauryl sulfate, tetrasodium pyrophosphate, hydrogen peroxide, etidronic acid, butylated hydroxytoluene, sodium saccharin, sucralose, phosphoric acid, water

STORAGE AND HANDLING

Store in a cool dry place. Keep tube capped when not in use.

Questions or comments? CALL 1-877-777-2743

MADE WITH PRIDE AND CARE FOR H-E-B®

SAN ANTONIO, TX 78204

PACKAGE LABEL

H-E-B®

Dazzling Mint

BRILLIANT WHITE

FLUORIDE ANTICAVITY TOOTHPASTE

NET WT. 5 OZ (141.7 g)